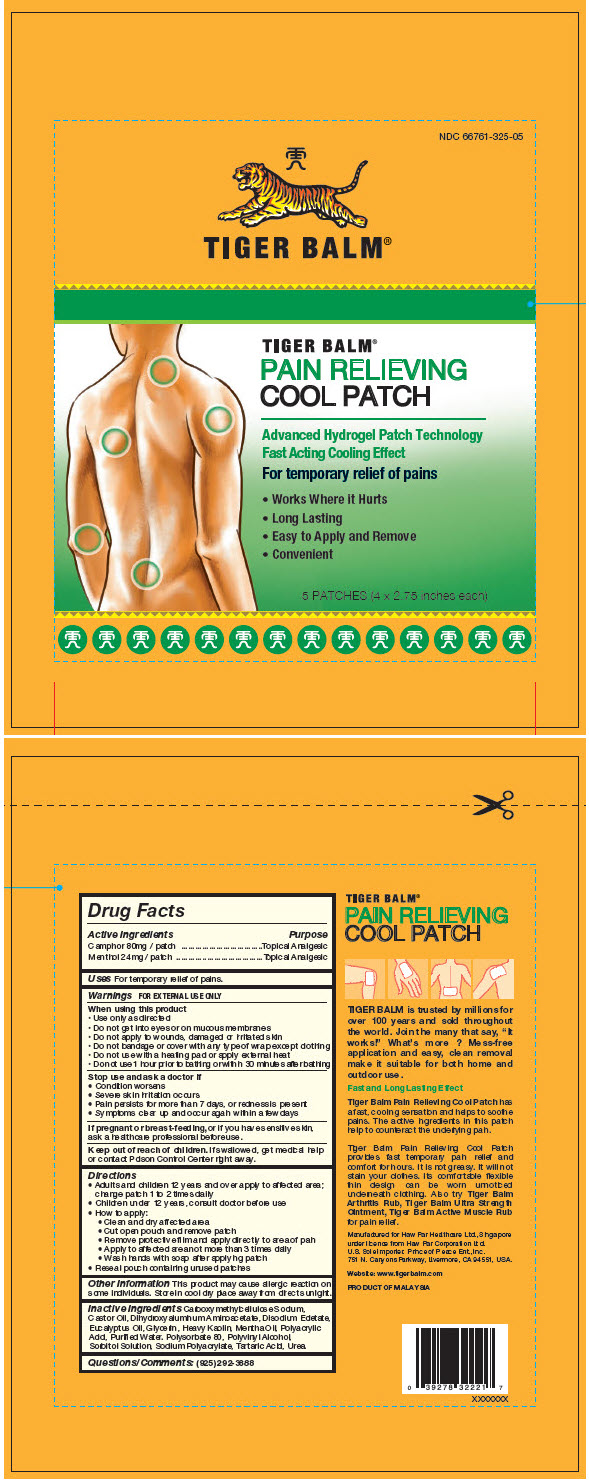 DRUG LABEL: Tiger Balm 
NDC: 66761-325 | Form: PATCH
Manufacturer: Haw Par Healthcare Ltd.
Category: otc | Type: HUMAN OTC DRUG LABEL
Date: 20241003

ACTIVE INGREDIENTS: Camphor (Synthetic) 80 mg/1 1; MENTHOL, UNSPECIFIED FORM 24 mg/1 1
INACTIVE INGREDIENTS: CARBOXYMETHYLCELLULOSE SODIUM, UNSPECIFIED; CASTOR OIL; DIHYDROXYALUMINUM AMINOACETATE; EDETATE DISODIUM; EUCALYPTUS OIL; GLYCERIN; KAOLIN; MENTHA ARVENSIS LEAF OIL; WATER; POLYSORBATE 80; POLYVINYL ALCOHOL, UNSPECIFIED; SORBITOL SOLUTION; TARTARIC ACID; UREA

Tiger Balm®
Pain Relieving Cool Patch

Drug Facts

ACTIVE INGREDIENT

Active Ingredients | Purpose
Camphor 80mg / patch | Topical Analgesic
Menthol 24mg / patch | Topical Analgesic

Uses

For temporary relief of pains.

Warnings

FOR EXTERNAL USE ONLY

When using this product

- Use only as directed
- Do not get into eyes or on mucous membranes
- Do not apply to wounds, damaged or irritated skin
- Do not bandage or cover with any type of wrap except clothing
- Do not use with a heating pad or apply external heat
- Do not use 1 hour prior to bathing or within 30 minutes after bathing

Stop use and ask a doctor if

- Condition worsens
- Severe skin irritation occurs
- Pain persists for more than 7 days, or redness is present
- Symptoms clear up and occur again within a few days

PREGNANCY OR BREAST FEEDING

If pregnant or breast-feeding, or if you have sensitive skin, ask a healthcare professional before use.

Keep out of reach of children. If swallowed, get medical help or contact Poison Control Center right away.

Directions

- Adults and children 12 years and over apply to affected area; change patch 1 to 2 times daily
- Children under 12 years, consult doctor before use
- How to apply:
  - Clean and dry affected area
  - Cut open pouch and remove patch
  - Remove protective film and apply directly to area of pain
  - Apply to affected area not more than 3 times daily
  - Wash hands with soap after applying patch
- Reseal pouch containing unused patches

Other Information

This product may cause allergic reaction on some individuals. Store in cool dry place away from direct sunlight.

Inactive Ingredients

Carboxymethylcellulose Sodium, Castor Oil, Dihydroxyaluminum Aminoacetate, Disodium Edetate, Eucalyptus Oil, Glycerin, Heavy Kaolin, Mentha Oil, Polyacrylic Acid, Purified Water. Polysorbate 80, Polyvinyl Alcohol, Sorbitol Solution, Sodium Polyacrylate, Tartaric Acid, Urea.

Questions/Comments

(925) 292-3888

PRINCIPAL DISPLAY PANEL - 5 Patch Packet

NDC 66761-325-05

TIGER BALM®

TIGER BALM®
PAIN RELIEVING
COOL PATCH

Advanced Hydrogel Patch Technology
Fast Acting Cooling Effect

For temporary relief of pains

- Works Where it Hurts
- Long Lasting
- Easy to Apply and Remove
- Convenient

5 PATCHES (4 x 2.75 inches each)